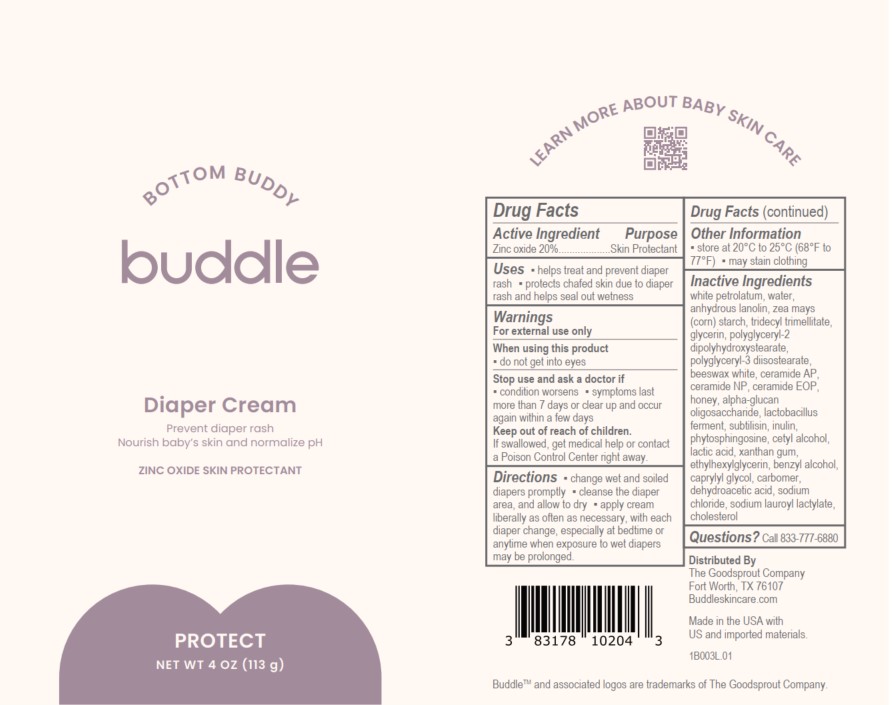 DRUG LABEL: Buddle Bottom Buddy Diaper Cream
NDC: 83178-102 | Form: CREAM
Manufacturer: The Goodsprout Company LLC
Category: otc | Type: HUMAN OTC DRUG LABEL
Date: 20241223

ACTIVE INGREDIENTS: ZINC OXIDE 20 g/100 g
INACTIVE INGREDIENTS: CETYL ALCOHOL; BENZYL ALCOHOL; DEHYDROACETIC ACID; WHITE PETROLATUM; CERAMIDE AP; SUBTILISIN; LACTIC ACID; CAPRYLYL GLYCOL; SODIUM CHLORIDE; POLYGLYCERYL-3 DIISOSTEARATE; .ALPHA.-GLUCAN OLIGOSACCHARIDE; WATER; CHOLESTEROL; XANTHAN GUM; LANOLIN; INULIN; PHYTOSPHINGOSINE; CARBOMER HOMOPOLYMER, UNSPECIFIED TYPE; CERAMIDE 1; LIMOSILACTOBACILLUS FERMENTUM; ETHYLHEXYLGLYCERIN; WHITE WAX; STARCH, CORN; TRIDECYL TRIMELLITATE; GLYCERIN; POLYGLYCERYL-2 DIPOLYHYDROXYSTEARATE; SODIUM LAUROYL LACTYLATE; CERAMIDE NP; HONEY

Active Ingredient

Zinc Oxide 20%

Purpose

Zinc oxide 20%...................Skin Protectant

Uses

- helps treat and prevent diaper rash
- protects chafed skin due to diaper rash and helps seal out wetness

Warnings

For external use only

When using this product

- do not get into eyes

Stop use and ask a doctor if

- condition worsens
- symptoms last more than 7 days or clear up and occur again within a few days

Keep out of reach of children.

If swallowed, get medical help or contact a Poison Control Center right away.

Directions

- change wet and soiled diapers promptly
- cleanse the diaper area, and allow to dry
- apply cream liberally as often as necessary, with each diaper change, especially at bedtime or anytime when exposure to wet diapers may be prolonged.

Other Information

- store at 20°C to 25°C (68°F to77°F)
- may stain clothing

Inactive Ingredients

white petrolatum, water, anhydrous lanolin, zea mays (corn) starch, tridecyl trimellitate, glycerin, polyglyceryl-2 dipolyhydroxystearate, polyglyceryl-3 diisostearate, beeswax white, ceramide AP, ceramide NP, ceramide EOP, honey, alpha-glucan oligosaccharide, lactobacillus ferment, subtilisin, inulin, phytosphingosine, cetyI alcohol, lactic acid, xanthan gum, ethylhexylglycerin, benzyl alcohol, caprylyl glycol, carbomer, dehydroacetic acid, sodium chloride, sodium lauroyl lactylate, cholesterol

Questions?

Call 833-777-6880

PACKAGE LABEL

Bottom Buddy

buddle

Diaper Cream

Prevent diaper rash

Nourish baby's skin and normalize pH

ZINC OXIDE SKIN PROTECTANT

PROTECT

NET WT 4 OZ (113 g)